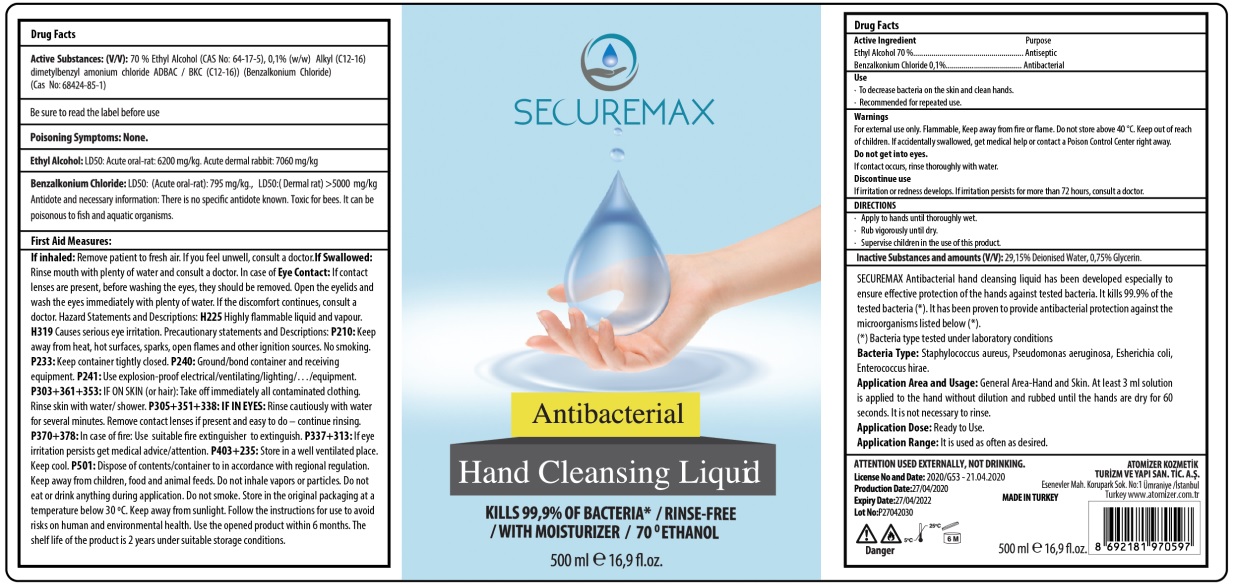 DRUG LABEL: SECUREMAX
NDC: 78092-602 | Form: SOLUTION
Manufacturer: ATOMIZER KOZMETIK TURIZM VE YAPI SANAYI TICARET ANONIM SIRKETI
Category: otc | Type: HUMAN OTC DRUG LABEL
Date: 20200527

ACTIVE INGREDIENTS: ALCOHOL 70 mL/100 mL; BENZALKONIUM CHLORIDE 0.1 g/100 mL
INACTIVE INGREDIENTS: WATER; GLYCERIN

SECUREMAX Antibacterial Hand Cleansing Solution

Active Ingredient

Ethyl Alcohol 70 %

Benzalkonium Chloride 0.1 %

Be sure to read the label before use.

Purpose

Antiseptic

Antibacterial

Use

- To decrease bacteria on the skin and clean hands.
- Recommended for repeated use.

Warnings

For external use only. Flammable, keep away from fire or flame. Do not store above 40°C.

Do not get into eyes.

If contact occurs, rinse thoroughly with water.

Discontinue use.

If irritation or redness develops. If irritation persists for more than 72 hours, consult a doctor.

Keep out of reach of children. If accidentally swallowed, get medical help or contact a Poison Control Center right away.

DIRECTIONS

- Apply to hands until thoroughly wet.
- Rub vigorously until dry.
- Supervise children in the use of this product.

Inactive Substances:

29,15% Deionised water, 0,75% Glycerin.

KILLS 99,9% OF BACTERIA* /RINSE-FREE /WITH MOISTURIZER /70 ^0ETHANOL

SECUREMAX Antibacterial hand cleansing liquid has been developed especially to ensure effective protection of the hands against tested bacteria. It kills 99.9% of the tested bacteria (*). It has been proven to provide antibacterial protection against the microorganisms listed below (*).

(*) Bacteria type tested under laboratory conditions

Bacteria Type: Staphylococcus aureus, Pseudomonas aeruginosa, Escherichia coli, Enterococcus hirae.

Application Area and Usage: General Area-Hand and Skin. At least 3 ml solution is applied to the hand without dilution and rubbed until the hands are dry for 60 seconds. It is not necessary to rinse.

Application Dose: Ready to Use.

Application Range: It is used as often as desired.

Poisoning Symptoms: None.

Ethyl Alcohol: LD50: Acute oral-rat: 6200 mg/kg. Acute dermal rabbit: 7060 mg/kg

Benzalkonium Chloride: LD50: (Acute oral-rat): 795 mg/kg., LD50:(Dermal rat)>5000 mg/kg

Antidote and necessary information: There is no specific antidote known. Toxic for bees. It can be poisonous to fish and aquatic organisms.

First Aid Measures:

If inhaled: Remove patient to fresh air. If you feel unwell, consult a doctor. If swallowed: Rinse mouth with plenty of water and consult a doctor. In case of Eye Contact: If contact lenses are present, before washing the eyes, they should be removed. Open the eyelids and wash the eyes immediately with plenty of water. If the discomfort continues, consult a doctor. Hazard Statements and Descriptions: H225 Highly flammable liquid and vapour. H319 Causes serious eye irritation. Precautionary statements and Descriptions: P210: Keep away from heat, hot surfaces, sparks, open flames and other ignition sources. No smoking. P233: Keep container tightly closed. P240: Ground/bond container and receiving equipment. P241: Use explosion-proof electrical/ventilating/lighting/.../equipment. P303+P361+P353: IF ON SKIN (or hair): Take off immediately all contaminated clothing. Rinse skin with water/ shower. P305+351+338: IF IN EYES: Rinse cautiously with water for several minutes. Remove contact lenses if present and easy to do - continue rinsing. P370+378: In case of fire: Use suitable fire extinguisher to extinguish. P337+P313: If eye irritation persists get medical advice/attention. P403+235: Store in a well-ventilated place. Keep cool. P501: Dispose of contents/container to in accordance with regional regulation. Keep away from children, food and animal feeds. Do not inhale vapors or particles. Do not eat or drink anything during application. Do not smoke. Store in the original packaging at a temperature below 30°C. Keep away from sunlight. Follow the instructions for use to avoid risks on human and environmental health. Use the opened product within 6 months. The shelf life of the product is 2 years under suitable storage conditions.

ATTENTION USED EXTERNALLY, NOT DRINKING.

Production Date:27/04/2020

Expiry Date:27/04/2020

ATOMİZER KOZMETİK TURİZM VE YAPI SAN. TİC. A.Ş.

Esenevler Mah. Korupark Sok. No:1 Ümraniye/İstanbul, Turkey www.atomizer.com.tr

MADE IN TURKEY